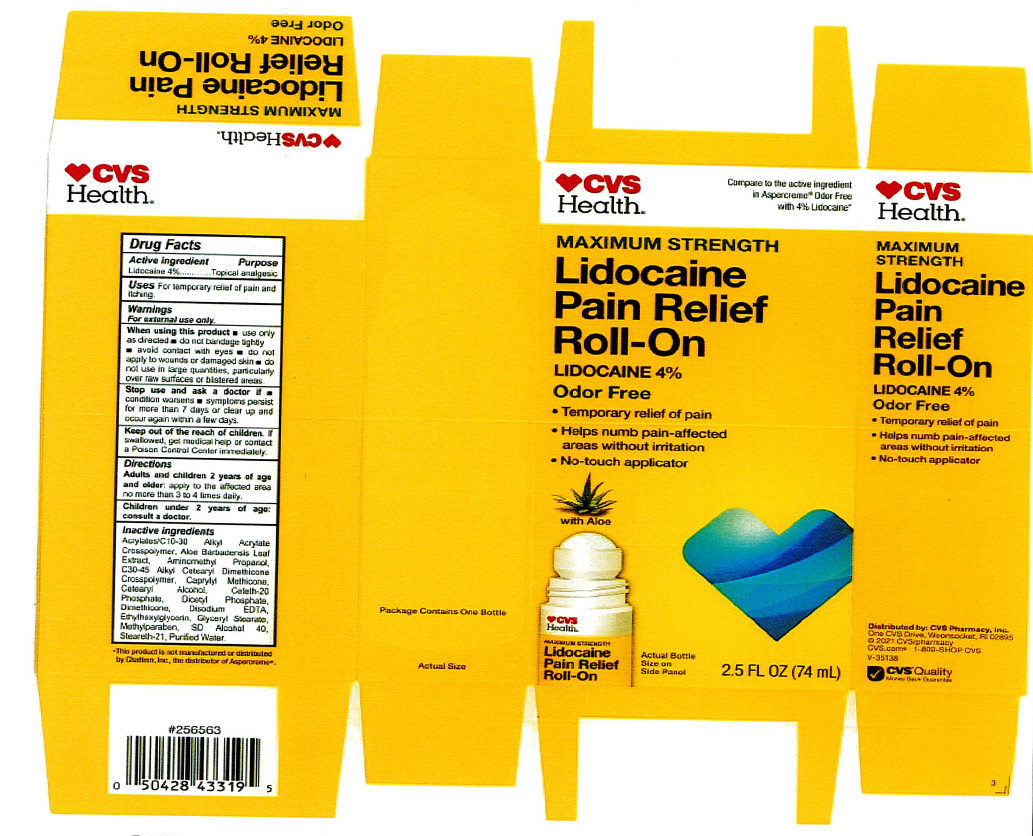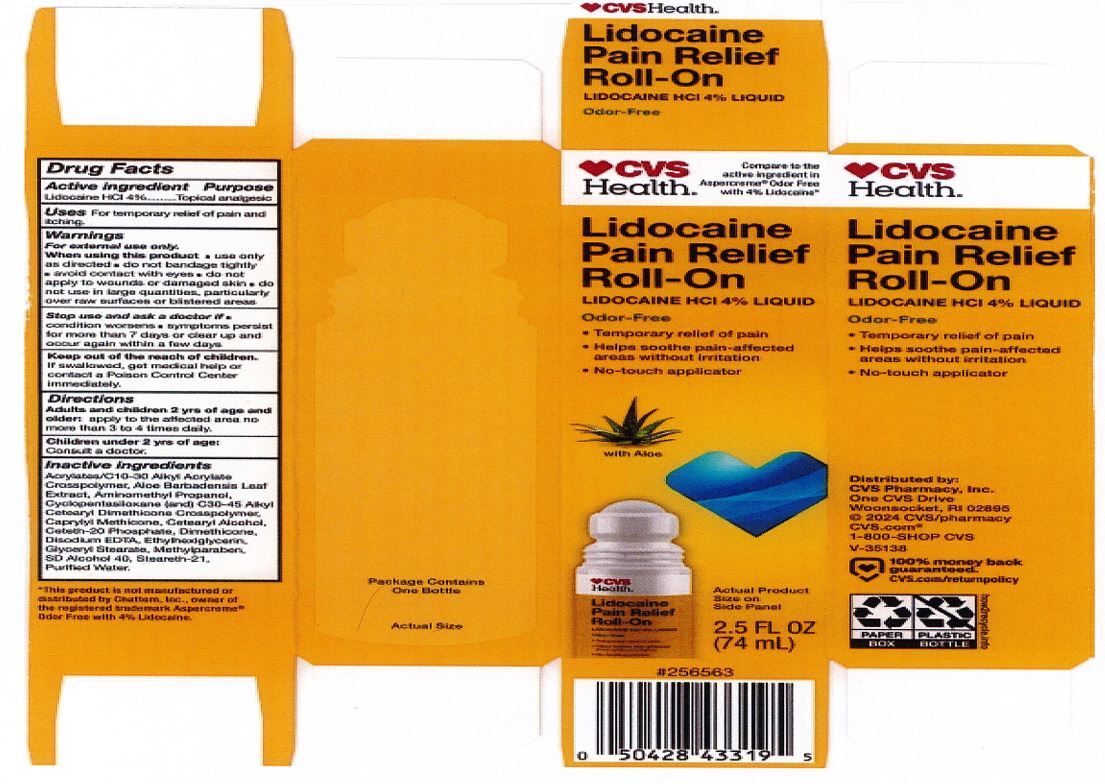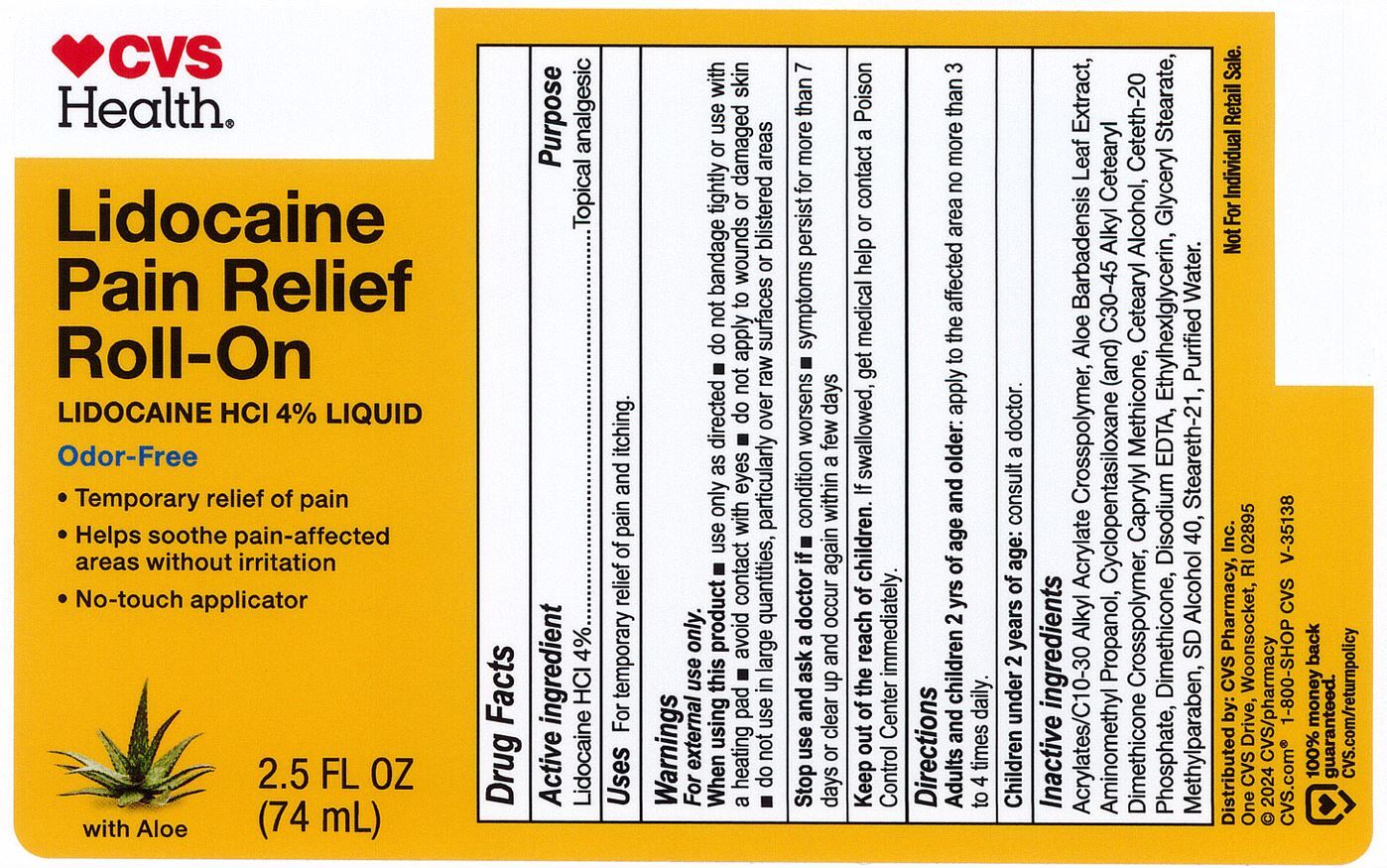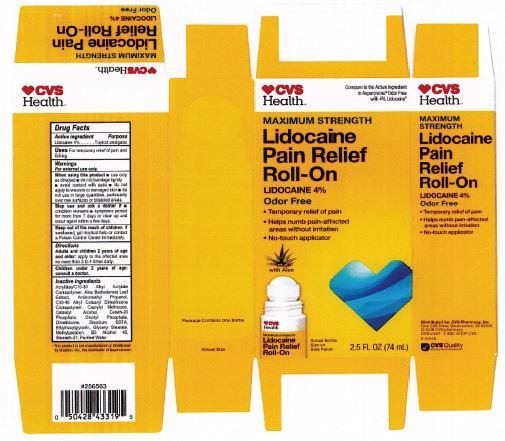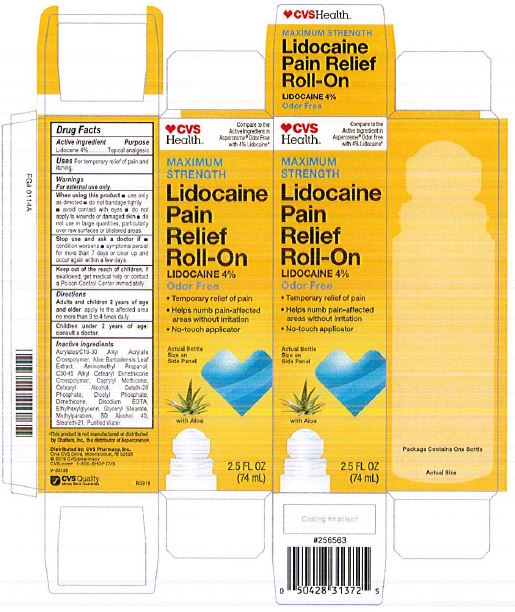 DRUG LABEL: Lidocaine Pain Relief Roll-On
NDC: 69842-029 | Form: LIQUID
Manufacturer: CVS Pharmacy
Category: otc | Type: HUMAN OTC DRUG LABEL
Date: 20241218

ACTIVE INGREDIENTS: LIDOCAINE HYDROCHLORIDE 4 g/100 mL
INACTIVE INGREDIENTS: AMINOMETHYLPROPANOL; WATER; STEARETH-21; ALCOHOL; METHYLPARABEN; CAPRYLYL TRISILOXANE; CARBOMER INTERPOLYMER TYPE A (55000 CPS); ALOE VERA LEAF; GLYCERYL MONOSTEARATE; ETHYLHEXYLGLYCERIN; EDETATE DISODIUM ANHYDROUS; DIHEXADECYL PHOSPHATE; DIMETHICONE; CETOSTEARYL ALCOHOL; HYDROXYETHYL ACRYLATE/SODIUM ACRYLOYLDIMETHYL TAURATE COPOLYMER (45000 MPA.S AT 1%); CETETH-20 PHOSPHATE

CVS Lido Roll-On

DOSAGE AND ADMINISTRATION

Adults and children 2 years of age and older: apply to the affected area no more than 3 to 4 times daily.

Children under 2 years of age: consult a doctor.

INACTIVE INGREDIENT

acrylates/C10-30 alkyl acrylate crosspolymer, aloe barbadensis leaf juice, aminomethyl propanol, C30-45 alkyl cetearyl dimethicone crosspolymer, caprylyl methicone, cetearyl alcohol, ceteth-20 phosphate, dicetyl phosphate, dimethicone, disodium EDTA, ethylhexylglycerin, glyceryl stearate, hydroxyethyl acrylate/sodium acryloyldimethyl taurate copolymer, methylparaben, polysorbate 60, SD alcohol 40 (15%), steareth-2, steareth-21, water

ACTIVE INGREDIENT

Lidocaine 4%

WARNINGS

For External Use Only.

When using this product:

use only as directed

do not bandage tightly or use with a heating pad

avoid contact with eyes

do not apply to wounds or damaged skin

do not use in large quantities

partifcularly over raw surfaces or blistered areas

Keep out of reach of children. If swallowed, get medical help or contact a Poison Control Center immediately.

INDICATIONS AND USAGE

For temporarily relief of pain and itching.

PURPOSE

Topical analgesic